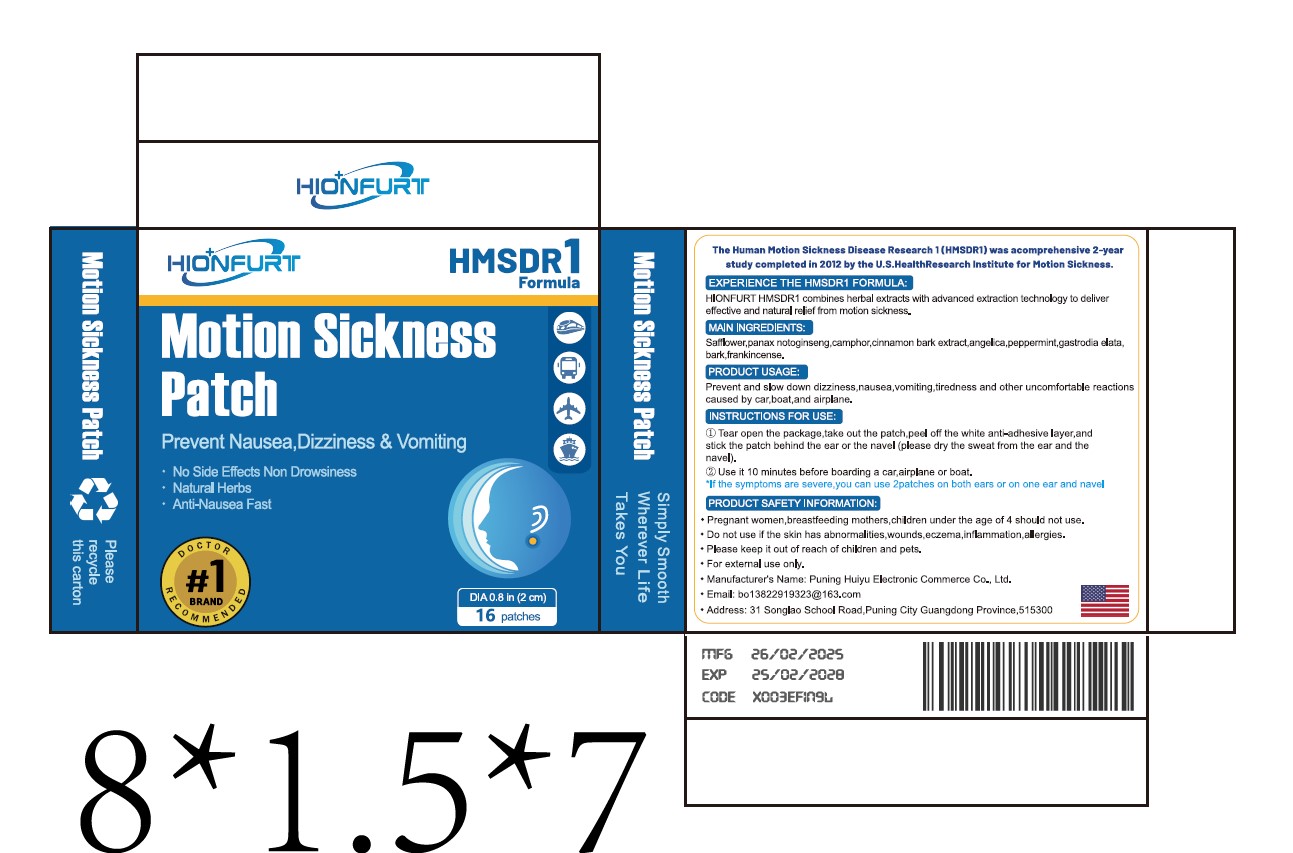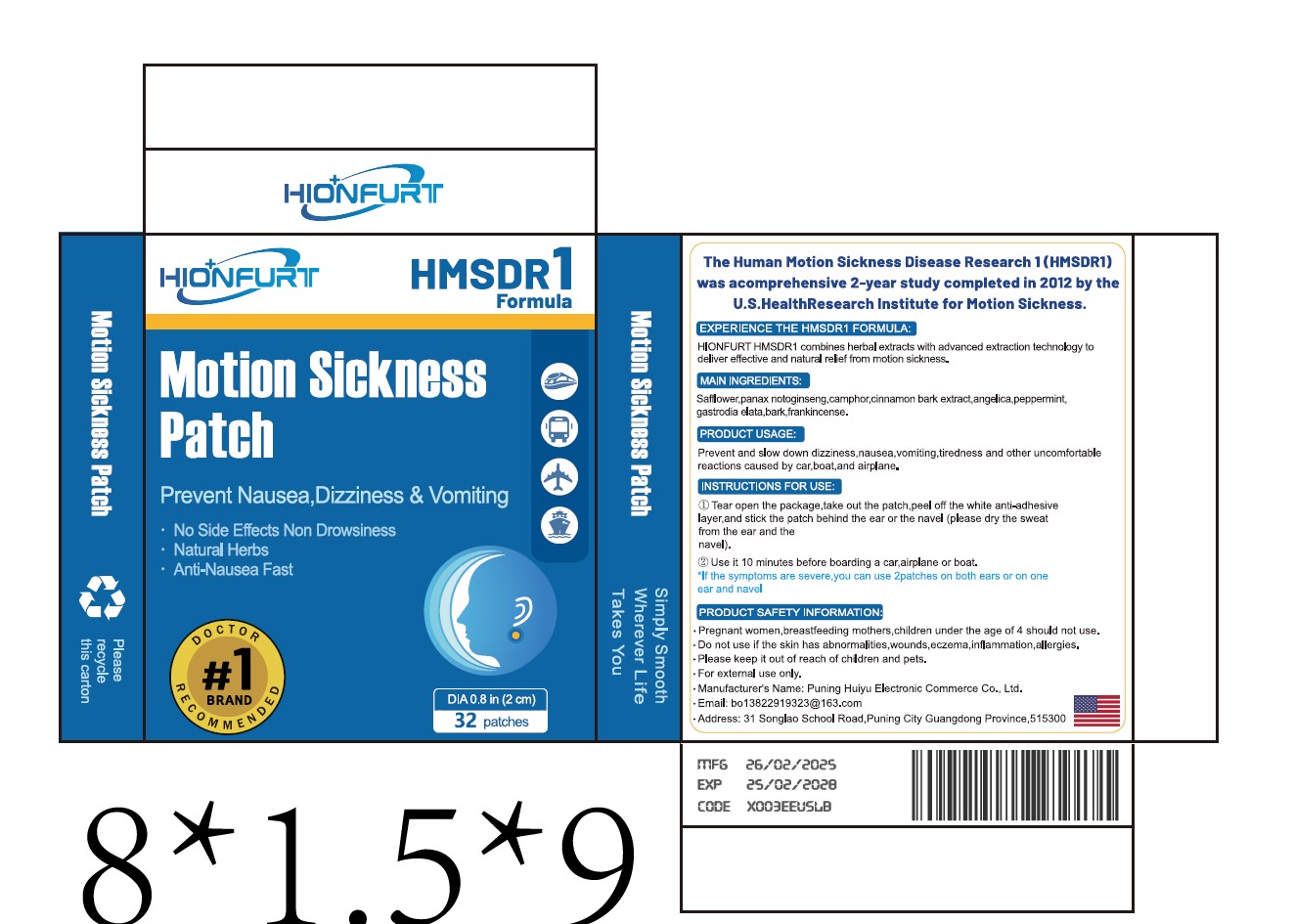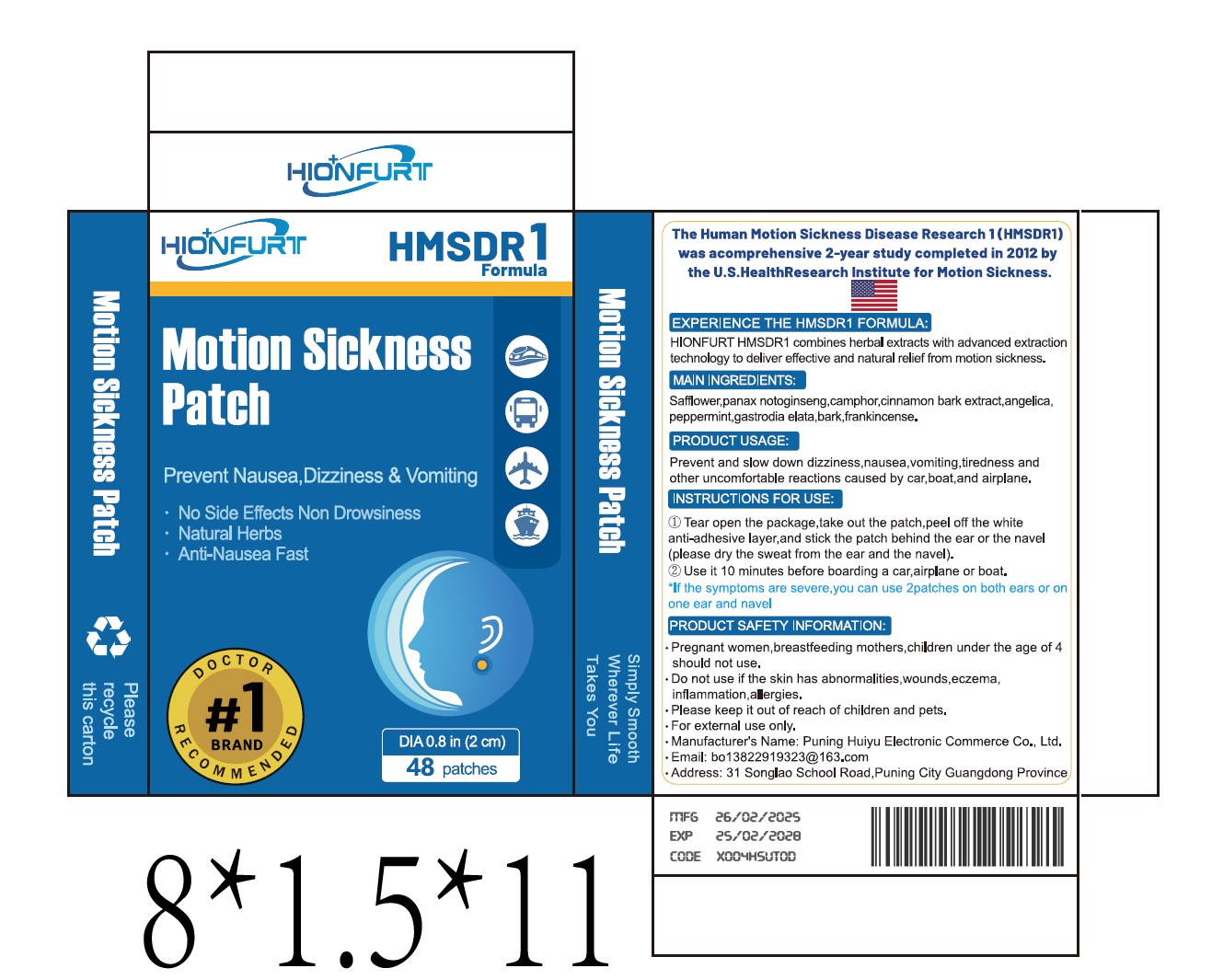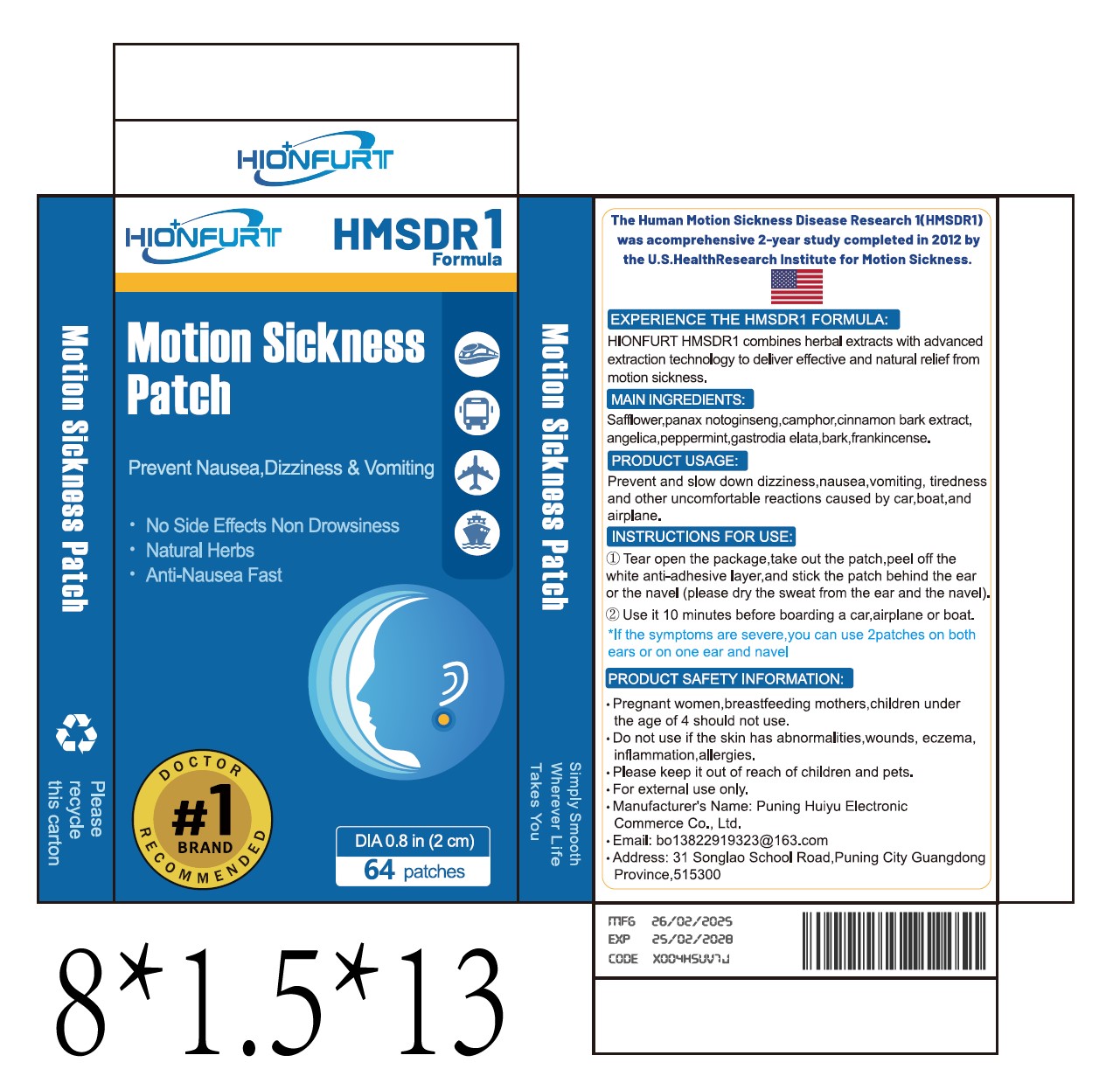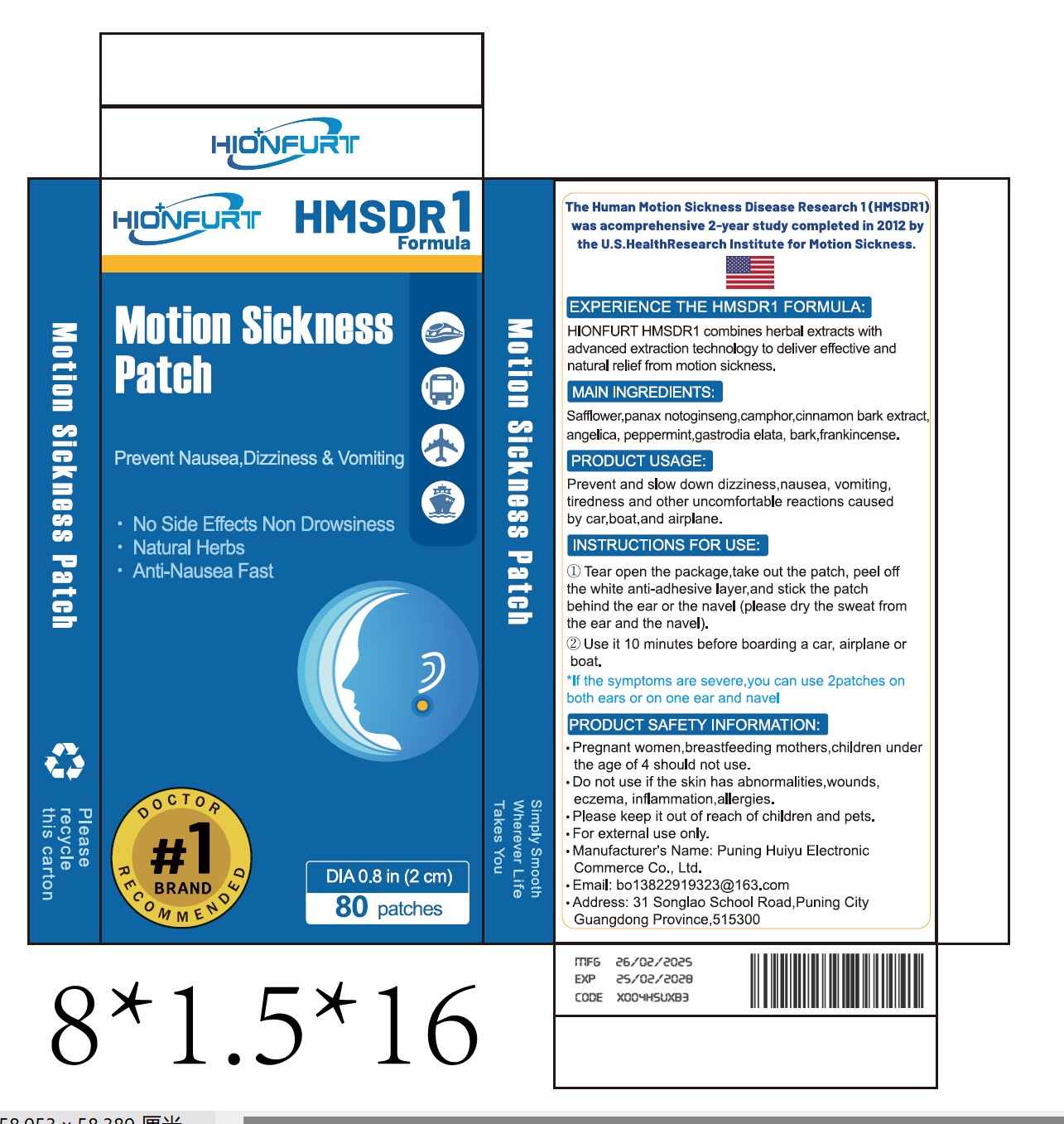 DRUG LABEL: HIONFURT Motion Sickness
NDC: 85213-005 | Form: PATCH
Manufacturer: Puning Huiyu E-Commerce Co., Ltd.
Category: otc | Type: HUMAN OTC DRUG LABEL
Date: 20250215

ACTIVE INGREDIENTS: CINNAMON OIL 10 mg/100 g; GASTRODIA ELATA WHOLE 5 mg/100 g; PEPPERMINT 20 mg/100 g; FRANKINCENSE 5 mg/100 g
INACTIVE INGREDIENTS: BETA-ADRENERGIC RECEPTOR KINASE 1; PANAX NOTOGINSENG WHOLE; CAMPHOR, (-)-; ANGELICA SEED; SAFFLOWER

Active ingredient

Cinnamon Bark Extract，Peppermint，Gastrodia elata，Frankincense

Inactive ingredients

Cinnamon Bark Extract，Peppermint，Gastrodia elata，Frankincense

Purpose

HIONFURT HMSDR1 combines herbal extracts withadvanced extraction technology to deliver effective andnatural relief from motion sickness.

When using this product

Prevent and slow down dizziness,nausea, vomitingtiredness and other uncomfortable reactions causedby car,boat,and airplane.

Do not use

Pregnant women,breastfeeding mothers,children underthe age of 4 should not use.Do not use if the skin has abnormalities,woundseczema,inflammation,allergies.

keep out of children

Please keep it out of reach of children and pets.
For external use only.

Dosage

Use it 10 minutes before boarding a car, airplane or boat.*lf the symptoms are severe,
you can use 2 patches on both ears or on one ear and navel

warning

Pregnant women, breastfeeding mothers,
children under the age of 4 should not use
.Do not use if the skin has abnormalities, wounds, eczema, inflammation, allergies.
Please keep it out of reach of children and pets.
For external use only.

Indication

1.Tear open the package, take out the patch, peel off the white anti-adhesive layer, and
stick the patchbehind the ear or the navel (please dry the sweat from the ear and the
navel).
2.Use it 10 minutes before boarding a car, airplane or boat.*lf the symptoms are severe,
you can use 2 patches on both ears or on one ear and navel